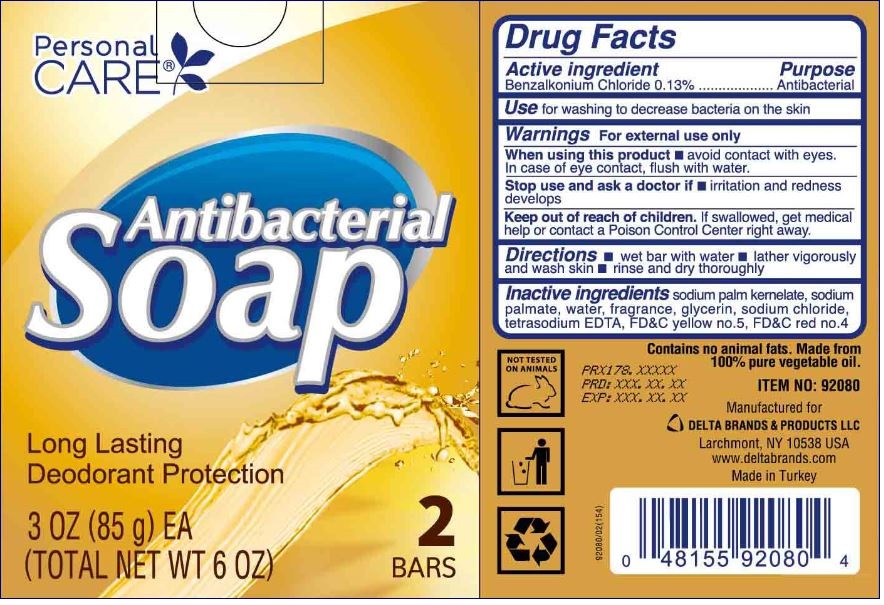 DRUG LABEL: Personal CARE
NDC: 72133-049 | Form: SOAP
Manufacturer: Delta Brands & Products, LLC
Category: otc | Type: HUMAN OTC DRUG LABEL
Date: 20201215

ACTIVE INGREDIENTS: BENZALKONIUM CHLORIDE 0.13 g/100 g
INACTIVE INGREDIENTS: SODIUM PALM KERNELATE; SODIUM PALMITATE; WATER; GLYCERIN; SODIUM CHLORIDE; EDETATE SODIUM; FD&C YELLOW NO. 5; FD&C RED NO. 4

Antibacterial Soap

Active ingredient

Benzalkonium Chloride 0.13%

Purpose

Antibacterial

Use

for washing to decrease bacteria on the skin

Warnings

For external use only

When using this product

■avoid contact with eyes. In case of eye contact, flush with water

Stop use and ask a doctor if

■ irritation and redness develops

Keep out of reach of children

If swallowed, get medical help or contact a Poison Control Center right away.

Directions

■ wet bar with water ■ lather vigorously and wash skin ■ rinse and dry thoroughly

Inactive ingredients

sodium palm kernelate, sodium palmate, water, fragrance, glycerin, sodium chloride, tetrasodium EDTA, FD&C yellow no. 5, FD&C red no. 4